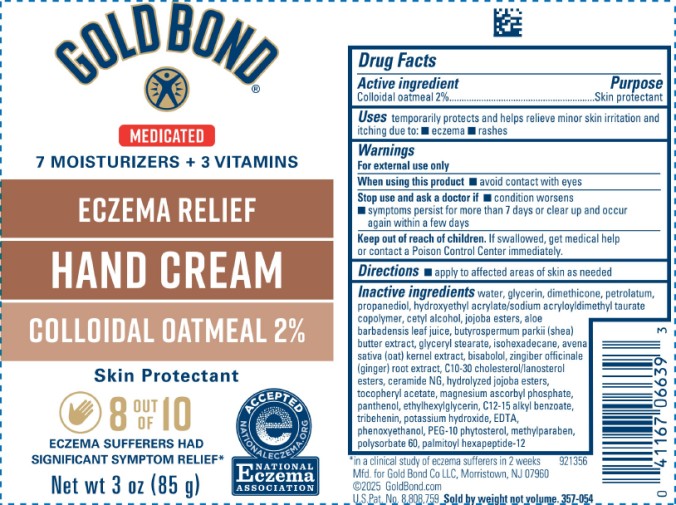 DRUG LABEL: Gold Bond Eczema Relief Medicated Hand Cream
NDC: 84714-0668 | Form: CREAM
Manufacturer: Gold Bond Co LLC
Category: otc | Type: HUMAN OTC DRUG LABEL
Date: 20251204

ACTIVE INGREDIENTS: OATMEAL 2 g/100 g
INACTIVE INGREDIENTS: WATER; GLYCERIN; DIMETHICONE; PETROLATUM; PROPANEDIOL; HYDROXYETHYL ACRYLATE/SODIUM ACRYLOYLDIMETHYL TAURATE COPOLYMER (100000 MPA.S AT 1.5%); CETYL ALCOHOL; JOJOBA OIL, RANDOMIZED; ALOE VERA LEAF; BUTYROSPERMUM PARKII (SHEA) BUTTER; GLYCERYL STEARATE; ISOHEXADECANE; OAT; BISABOLOL; GINGER; C10-30 CHOLESTEROL/LANOSTEROL ESTERS; CERAMIDE NG; HYDROLYZED JOJOBA ESTERS (ACID FORM); ALPHA-TOCOPHEROL ACETATE; MAGNESIUM ASCORBYL PHOSPHATE; PHOSPHATE ION; PANTHENOL; ETHYLHEXYLGLYCERIN; ALKYL (C12-15) BENZOATE; TRIBEHENIN; POTASSIUM HYDROXIDE; EDETIC ACID; PHENOXYETHANOL; METHYLPARABEN; POLYSORBATE 60; PALMITOYL HEXAPEPTIDE-12

Gold Bond Eczema Relief Hand Cream

Active ingredient

Colloidal oatmeal 2%

Purpose

Skin protectant

Uses

temporarily protects and helps relieve minor skin irritation and itching due to:

■ eczema ■ rashes

Warnings

For external use only

When using this product

■ avoid contact with eyes

Stop use and ask a doctor if

■ condition worsens

■ symptoms persist for more than 7 days or clear up and occur again within a few days

Keep out of reach of children.

If swallowed, get medical help or contact a Poison Control Center immediately.

Directions

■ apply to affected areas of skin as needed

Inactive ingredients

water, glycerin, dimethicone, petrolatum, propanediol, hydroxyethyl acrylate/sodium acryloyldimethyl taurate copolymer, cetyl alcohol, jojoba esters, aloe barbadensis leaf juice, butyrospermum parkii (shea) butter extract, glyceryl stearate, isohexadecane, avena sativa (oat) kernel extract, bisabolol, zingiber officinale (ginger) root extract, C10-30 cholesterol/lanosterol esters, ceramide NG, hydrolyzed jojoba esters, tocopheryl acetate, magnesium ascorbyl phosphate, panthenol, ethylhexylglycerin, C12-C15 alkyl benzoate, tribehenin, potassium hydroxide, EDTA, phenoxyethanol, PEG-10 phytosterol, methylparaben, polysorbate 60, palmitoyl hexapeptide-12

PRINCIPAL DISPLAY PANEL

GOLD BOND
ECZEMA RELIEF
HAND CREAM
COLLOIDAL OATMEAL 2%
Skin Protectant
Net wt 3 oz (85 g)